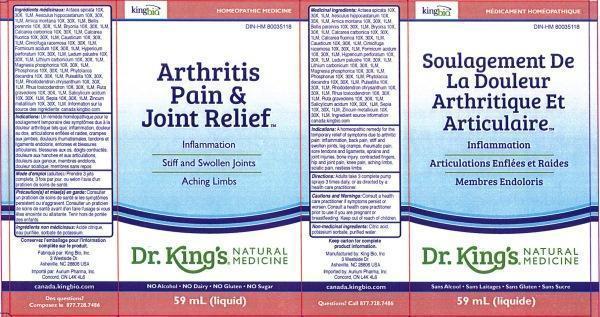 DRUG LABEL: Arthritis Pain and Joint Relief / Soulagement De La Douleur Arthritique Et Articulaire
NDC: 57955-1804 | Form: LIQUID
Manufacturer: King Bio Inc.
Category: homeopathic | Type: HUMAN OTC DRUG LABEL
Date: 20140821

ACTIVE INGREDIENTS: ACTAEA SPICATA ROOT 10 [hp_X]/59 mL; HORSE CHESTNUT 10 [hp_X]/59 mL; ARNICA MONTANA 10 [hp_X]/59 mL; BELLIS PERENNIS 10 [hp_X]/59 mL; BRYONIA ALBA ROOT 10 [hp_X]/59 mL; OYSTER SHELL CALCIUM CARBONATE, CRUDE 10 [hp_X]/59 mL; CALCIUM FLUORIDE 10 [hp_X]/59 mL; CAUSTICUM 10 [hp_X]/59 mL; BLACK COHOSH 10 [hp_X]/59 mL; FORMIC ACID 10 [hp_X]/59 mL; HYPERICUM PERFORATUM 10 [hp_X]/59 mL; LEDUM PALUSTRE TWIG 10 [hp_X]/59 mL; LITHIUM CARBONATE 10 [hp_X]/59 mL; MAGNESIUM PHOSPHATE, DIBASIC TRIHYDRATE 10 [hp_X]/59 mL; PHOSPHORUS 10 [hp_X]/59 mL; PHYTOLACCA AMERICANA ROOT 10 [hp_X]/59 mL; PULSATILLA VULGARIS 10 [hp_X]/59 mL; RHODODENDRON AUREUM LEAF 10 [hp_X]/59 mL; TOXICODENDRON PUBESCENS LEAF 10 [hp_X]/59 mL; RUTA GRAVEOLENS FLOWERING TOP 10 [hp_X]/59 mL; SALICYLIC ACID 10 [hp_X]/59 mL; SEPIA OFFICINALIS JUICE 10 [hp_X]/59 mL; ZINC 10 [hp_X]/59 mL
INACTIVE INGREDIENTS: CITRIC ACID MONOHYDRATE; POTASSIUM SORBATE; WATER

Arthritis Pain and Joint Relief Soulagement De La Douleur Arthritique Et Articulaire

ACTIVE INGREDIENT

Medicinal ingredients/Ingrédients médicinaux: Actaea spicata 10X, 30X, 1LM, Aesculus hippocastanum 10X, 30X, 1LM, Arnica montana 10X, 30X, 1LM, Bellis perennis 10X, 30X, 1LM, Bryonia 10X, 30X, 1LM, Calcarea carbonica 10X, 30X, 1LM, Calcarea fluorica 10X, 30X, 1LM, Causticum 10X, 30X, 1LM, Cimicifuga racemosa 10X, 30X, 1LM, Formicum acidum 10X, 30X, 1LM, Hypericum perforatum 10X, 30X, 1LM, Ledum palustre 10X, 30X, 1LM, Lithium carbonicum 10X, 30X, 1LM, Magnesia phosphorica 10X, 30X, 1LM, Phosphorus 10X, 30X, 1LM, Phytolacca decandra 10X, 30X, 1LM, Pulsatilla 10X, 30X, 1LM, Rhododendron chrysanthum 10X, 30X, 1LM, Rhus toxicodendron 10X, 30X, 1LM, Ruta graveolens 10X, 30X, 1LM, Salicylicum acidum 10X, 30X, 1LM, Sepia 10X, 30X, 1LM, Zincum metallicum 10X, 30X, 1LM. Ingredient source information: canada.kingbio.com

INACTIVE INGREDIENT

Non-medicinal ingredients: Citric acid, Potassium sorbate, purified water.

Ingrédients non médicinaux: Acide citrique, eau purifiée, sorbate de potassium.

PURPOSE

Indications: A homeopathic remedy for the temporary relief of symptoms due to arthritic pain: inflammation, back pain, stiff and swollen joints, leg cramps, rheumatic pain, sore tendons and ligaments, sprains and joint injuries, bone injury, contracted fingers, hip and joint pain, knee pain, aching limbs, sciatic pain, restless limbs.

Indications: un remède homéopathique pour le soulagement temporaire des symptômes dus à la douleur arthritique tels que: inflammation, douleur au dos, articulations enflées et raides, crampes aux jambes, douleurs rhumatismales, tendons et ligaments endoloris, entorses et blessures articulaires, blessures aux os, doigts contractês,douleurs aux hanches et aux articulations, douleurs aux genoux, membres endoloris, douleur sciatique, membres sans repos.

DOSAGE AND ADMINISTRATION

Directions: Adults take 3 complete pump sprays, 3 times daily, or as directed by a health care practitioner.

Mode d'emploi (adultes): prendre 3 jets complets, 3 fois par jour, ou selon l'avis d'un praticien de soins de santé.

INDICATIONS AND USAGE

Indications: A homeopathic remedy for the temporary relief of symptoms due to arthritic pain:

- inflammation
- back pain
- stiff and swollen joints
- leg cramps
- rheumatic pain
- sore tendons and ligaments
- sprains and join injuries
- bone injury
- contracted fingers
- hip and joint pain
- knee pain
- aching limbs
- sciatic pain
- restless limbs

Indications: un remède homéopathique pour le soulagement temporaire des symptômes dus à la douleur arthritique tels que:

- inflammation
- douleur au dos
- articulations enflées et raides
- crampes aux jambes
- douleurs rhumatismales
- tendons et ligaments endoloris
- entorses et blessures articulaires
- blessures aux os
- doigts contractés
- douleurs aux genoux
- membres endoloris
- douleur sciatique
- membres sans repos

WARNINGS

Cautions and Warnings: Consult a health care practitioner if symptoms persist or worsen. Consult a health care practitioner prior to use if you are pregnant or breastfeeding.

Précaution(s) et mise(s) en garde: Consulter un praticien de soins de santé si les symptômes persistent ou s'aggravent. Consulter un praticien de soins de santé avant d'en faire l'usage si vous êtes enceinte ou allaitante.

Keep out of reach of children.

Tenir hors de portée des enfants.